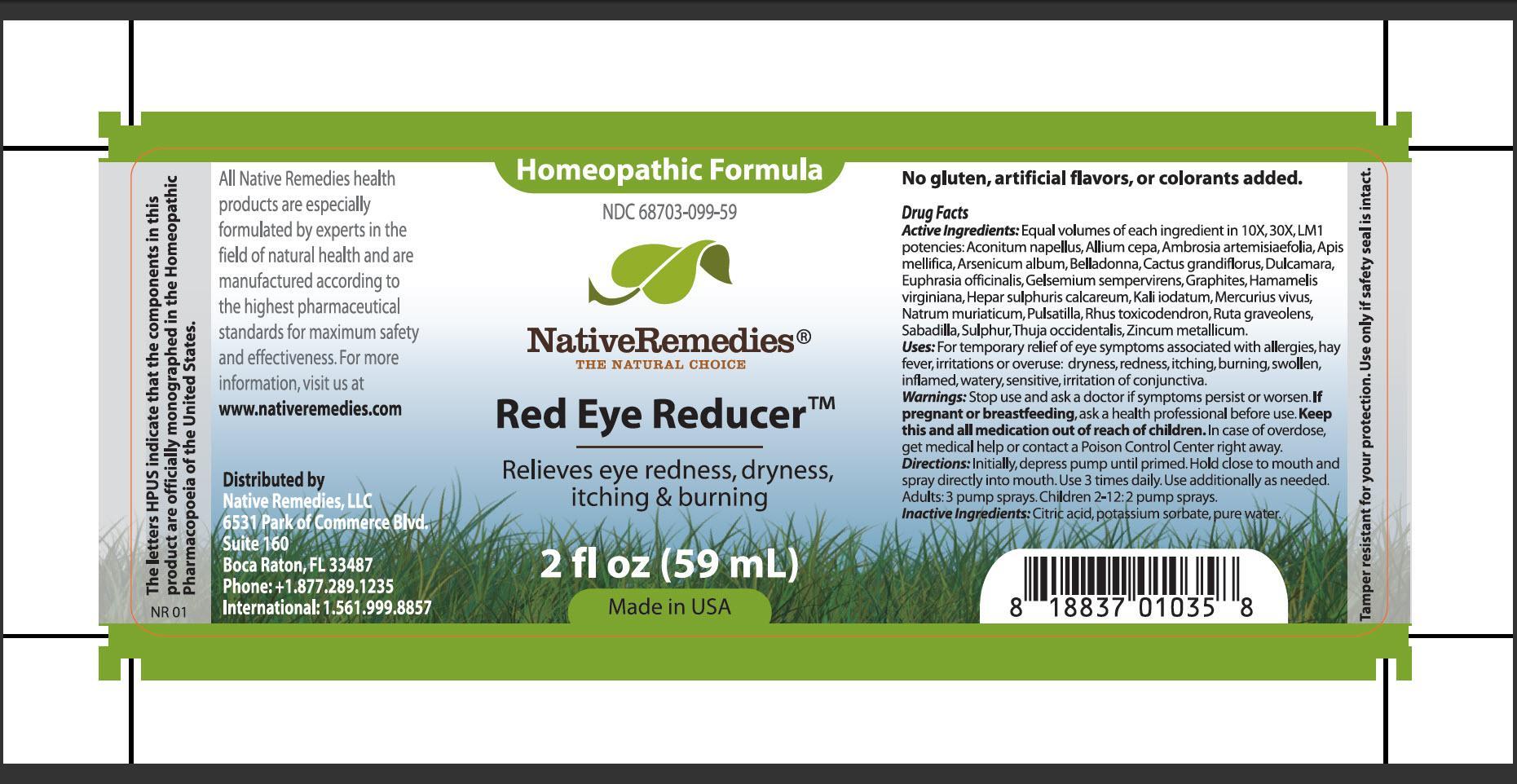 DRUG LABEL: Red Eye Reducer
NDC: 68703-099 | Form: SPRAY
Manufacturer: Native Remedies, LLC
Category: homeopathic | Type: HUMAN OTC DRUG LABEL
Date: 20130717

ACTIVE INGREDIENTS: ACONITUM NAPELLUS 10 [hp_X]/59 mL; ONION 10 [hp_X]/59 mL; AMBROSIA ARTEMISIIFOLIA 10 [hp_X]/59 mL; APIS MELLIFERA 10 [hp_X]/59 mL; ARSENIC TRIOXIDE 10 [hp_X]/59 mL; ATROPA BELLADONNA 10 [hp_X]/59 mL; SELENICEREUS GRANDIFLORUS STEM 10 [hp_X]/59 mL; SOLANUM DULCAMARA TOP 10 [hp_X]/59 mL; EUPHRASIA STRICTA 10 [hp_X]/59 mL; GELSEMIUM SEMPERVIRENS ROOT 10 [hp_X]/59 mL; GRAPHITE 10 [hp_X]/59 mL; HAMAMELIS VIRGINIANA ROOT BARK/STEM BARK 10 [hp_X]/59 mL; CALCIUM SULFIDE 10 [hp_X]/59 mL; POTASSIUM IODIDE 10 [hp_X]/59 mL; MERCURY  10 [hp_X]/59 mL; SODIUM CHLORIDE 10 [hp_X]/59 mL; PULSATILLA VULGARIS 10 [hp_X]/59 mL; TOXICODENDRON PUBESCENS LEAF  10 [hp_X]/59 mL; RUTA GRAVEOLENS FLOWERING TOP 10 [hp_X]/59 mL; SCHOENOCAULON OFFICINALE SEED 10 [hp_X]/59 mL; SULFUR 10 [hp_X]/59 mL; THUJA OCCIDENTALIS LEAFY TWIG 10 [hp_X]/59 mL; ZINC 10 [hp_X]/59 mL
INACTIVE INGREDIENTS: CITRIC ACID MONOHYDRATE; POTASSIUM SORBATE; WATER

Red Eye Reducer

PURPOSE

Relieves eye redness, dryness, itching and burning

Drug Facts
Active Ingredients: Equal volumes of each ingredient in 10X, 30X, LM1 potencies: Aconitum napellus, Allium cepa, Ambrosia artemisiaefolia, Apis mellifica, Arsenicum album, Belladonna, Cactus grandiflorus, Dulcamara, Euphrasia officinalis, Gelsemium sempervirens, Graphites, Hamamelis virginiana, Hepar sulphuris calcareum, Kali iodatum, Mercurius vivus, Natrum muriaticum, Pulsatilla, Rhus toxicodendron, Ruta graveolens, Sabadilla, Sulphur, Thuja occidentalis, Zincum metallicum

INDICATIONS AND USAGE

Uses: For temporary relief of eyes symptoms associated with allergies, high fever, irritations or overuse: dryness, redness, itching, burning, swollen, inflamed, watery, sensitive, irritation of conjunctiva

WARNINGS

Warnings: Stop use and ask a doctor if symptoms persist or worsen

PREGNANCY OR BREAST FEEDING

If pregnant or breastfeeding, ask a health professional before use

KEEP OUT OF REACH OF CHILDREN

Keep this and all medication out of reach of children

OVERDOSAGE

In case of overdose, get medical help or contact a Poison Control Center right away

DOSAGE AND ADMINISTRATION

Directions: Initially, depress pump until primed. Hold close to mouth and spray directly into mouth. Use 3 times daily. Use additionally as needed. Adults: 3 pump sprays. Children 2-12: 2 pump sprays

Inactive Ingredients: Citric acid, potassium sorbate, pure water

PATIENT COUNSELING INFORMATION

The letters HPUS indicate that the components in this product are officially monographed in the Homeopathic Pharmacopoeia of the United States.

All Native Remedies health products are especially formulated by experts in the field of natural health and are manufactured according to the highest pharmaceutical standards for maximum safety and effectiveness. For more information, visit us at www.nativeremedies.com

Distributed by
Native Remedies, LLC
6531 Park of Commerce Blvd.
Suite 160
Boca Raton, FL 33487
Phone: +1.877.289.1235
International: 1.561.999.8857

No gluten artificial flavors, or colorants added

STORAGE AND HANDLING

Tamper resistant for your protection. Use only if safety seal is intact